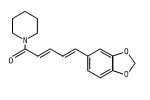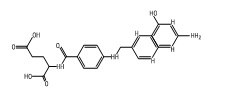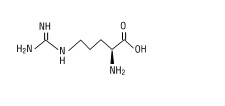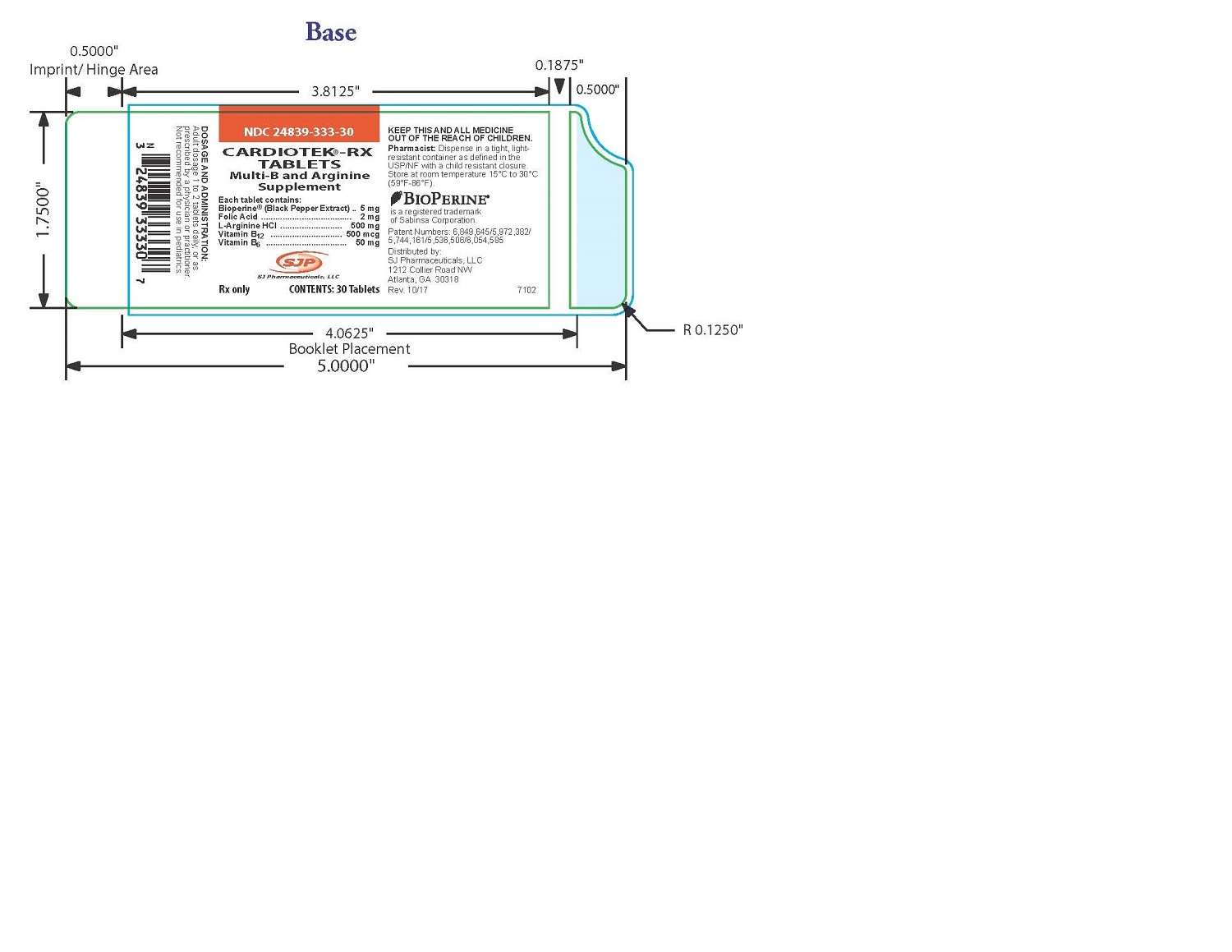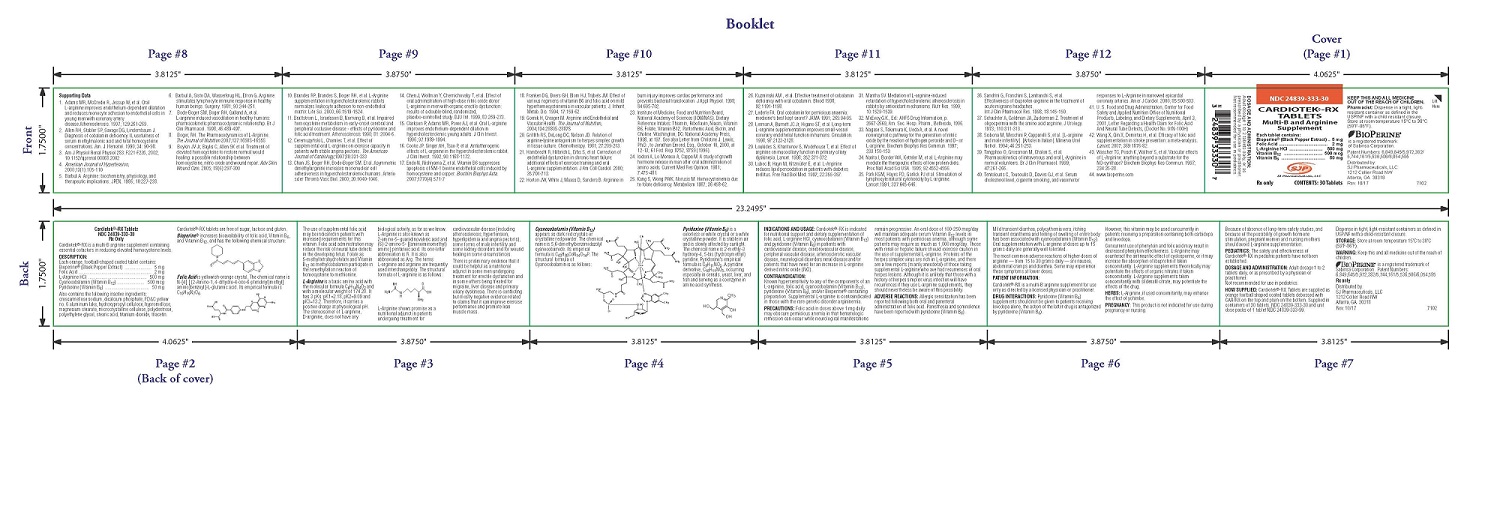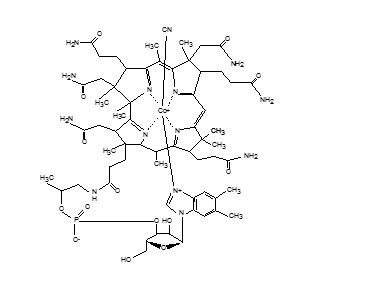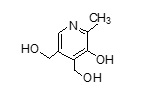 DRUG LABEL: CARDIOTEK-RX
NDC: 24839-333 | Form: TABLET, COATED
Manufacturer: SJ PHARMACEUTICALS, LLC
Category: other | Type: DIETARY SUPPLEMENT
Date: 20180426

ACTIVE INGREDIENTS: BLACK PEPPER 5 mg/58 mg; FOLIC ACID 2 mg/58 mg; ARGININE .5 mg/58 mg; CYANOCOBALAMIN .5 mg/58 mg; PYRIDOXINE 50 mg/58 mg

CARDIOTEK-RX

DESCRIPTION:

Cardiotek®-RX is a multi-B arginine supplement containing
essential cofactors in reducing elevated homocysteine levels.

DESCRIPTION:

Each orange, football-shaped coated tablet contains:
Bioperine® (Black Pepper Extract) ...................... 5 mg
Folic Acid ............................................................ 2 mg
L-Arginine HCl ................................................ 500 mg
Cyanocobalamin (Vitamin B12) ...................... 500 mcg
Pyridoxine (Vitamin B6) .................................... 50 mg
Also contains the following inactive ingredients:
croscarmellose sodium, dicalcium phosphate, FD&C yellow
no. 6 aluminum lake, hydroxypropyl cellulose, hypromellose,
magnesium stearate, microcrystalline cellulose, polydextrose,
polyethylene glycol, stearic acid, titanium dioxide, triacetin.
Cardiotek®-RX tablets are free of sugar, lactose and gluten.

Bioperine® increases bioavailability of folic acid, Vitamin B6,
and Vitamin B12, and has the following chemical structure:

Folic Acid is yellowish-orange crystal. The chemical name is
N-[4[ [ (2-Amino-1, 4-dihydro-4-oxo-6-pteridinyl)methyl]
amino]benzoyl]-L-glutamic acid. Its empirical formula is
C19H19N7O6.
The use of supplemental folic acid
may be indicated in patients with
increased requirements for this
vitamin. Folic acid administration may
reduce the risk of neural tube defects
in the developing fetus. Folate as
5-methyltetrahydrofolate and Vitamin
B12 as methylcobalamin participate in
the remethylation reaction of
homocysteine to methionine.

L-Arginine is a basic amino acid with
the molecular formula C6H14N4O2 and
with a molecular weight of 174.20. It
has 3 pKs: pK1=2.18, pK2=9.09 and
pK3=13.2. Therefore, it carries a
positive charge at physiological pH.
The stereoisomer of L-arginine,
D-arginine, does not have any
biological activity, as far as we know.
L-Arginine is also known as
2-amino-5- guanidinovaleric acid and
(S)-2-amino-5- [(aminoiminomethyl)
amino] pentanoic acid. Its one-letter
abbreviation is R. It is also
abbreviated as Arg. The terms
L-arginine and arginine are frequently
used interchangeably. The structural
formula of L-arginine is as follows:

L-Arginine shows promise as a
nutritional adjunct in patients
undergoing treatment for
cardiovascular disease (including
atherosclerosis, hypertension,
hyperlipidemia and angina pectoris),
some forms of male infertility and
some kidney disorders and for wound
healing in some circumstances.
There is preliminary evidence that it
could be helpful as a nutritional
adjunct in some men undergoing
treatment for erectile dysfunction and
in some others being treated for
migraine, liver disease and primary
ciliary dyskinesia. There is conflicting
but mostly negative evidence related
to claims that it can improve exercise
performance and promote lean
muscle mass.
Cyanocobalamin (Vitamin B12)
appears as dark red crystals or
crystalline red powder. The chemical
name is 5,6-dimethylbenzimidazolyl
cyanocobamide. Its empirical
formula is C63H88CoN14O14P. The
structural formula of
Cyanocobalamin is as follows:

Pyridoxine (Vitamin B6) is a
colorless or white crystal or a white
crystalline powder. It is stable in air
and is slowly affected by sunlight.
The chemical name is 2-methly-3
hydroxy-4, 5-bis (hydroxymethyl)
pyridine. Pyridoxine’s empirical
formula is C8H11NO3. A pyridine
derivative, C18H11NO3, occurring
especially in cereals, yeast, liver, and
fish and serving as a coenzyme in
amino acid synthesis.

PRECAUTIONS:

Folic acid in doses above 1 mg daily
may obscure pernicious anemia in that hematologic
remission can occur while neurological manifestations
remain progressive. An oral dose of 100-250 mcg/day
will maintain adequate serum Vitamin B12 levels in
most patients with pernicious anemia, although some
patients may require as much as 1,000 mcg/day. Those
with renal or hepatic failure should exercise caution in
the use of supplemental L-arginine. Proteins of the
herpes simplex virus are rich in L-arginine, and there
are a few reports (mainly anecdotal) of those taking
supplemental L-arginine who ave had recurrences of oral
herpes lesions. Although it is unlikely that those with a
history of herpes simplex virus infection will have
recurrences if they use L-arginine supplements, they
should nevertheless be aware of this possibility.

DOSAGE AND ADMINISTRATION:

Adult dosage 1 to 2
tablets daily, or as prescribed by a physician or
practitioner.
Not recommended for use in pediatrics.

WARNING:

Keep this and all medicine out of the reach of
children.
is a registered trademark of
Sabinsa Corporation. Patent Numbers:
6,849,645/5,972,382/5,744,161/5,536,506/6,054,585
Rx only
Distributed by:
SJ Pharmaceuticals, LLC
1212 Collier Road NW
Atlanta, GA 30318
Rev. 10/17 7102

PACKAGE LABEL

NDC 24839-333-30
CARDIOTEK®-RX TABLETS
Multi-B and Arginine Supplement
Each tablet contains:
Bioperine® (Black Pepper Extract) .. 5 mg
Folic Acid ...................................... 2 mg
L-Arginine HCl .......................... 500 mg
Vitamin B12 .............................. 500 mcg
Vitamin B6 .................................. 50 mg

SJ Pharmaceuticals, LLC

Rx only CONTENTS: 30 Tablets

DOSAGE AND ADMINISTRATION:
Adult dosage 1 to 2 tablets daily, or as
prescribed by a physician or practitioner.
Not recommended for use in pediatrics.

KEEP THIS AND ALL MEDICINE
OUT OF THE REACH OF CHILDREN.
Pharmacist: Dispense in a tight, lightresistant
container as defined in the
USP/NF with a child resistant closure.
Store at room temperature 15°C to 30°C
(59°F-86°F).
BIOPERINE®
is a registered trademark
of Sabinsa Corporation.

Patent Numbers: 6,849,645/5,972,382/
5,744,161/5,536,506/6,054,585
Distributed by:
SJ Pharmaceuticals, LLC
1212 Collier Road NW
Atlanta, GA 30318
Rev. 10/17